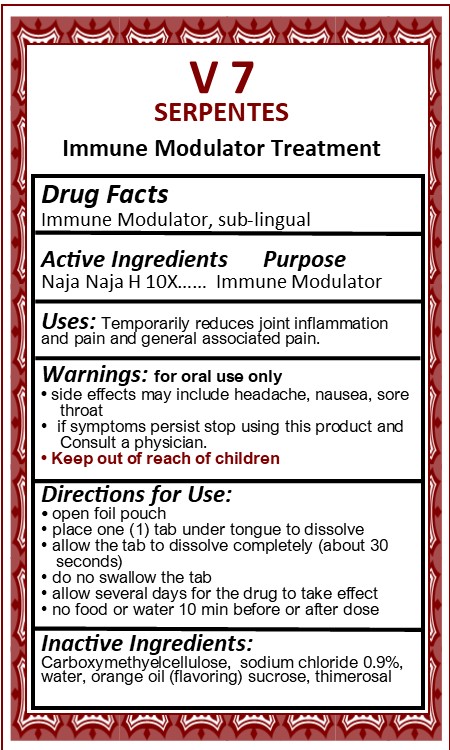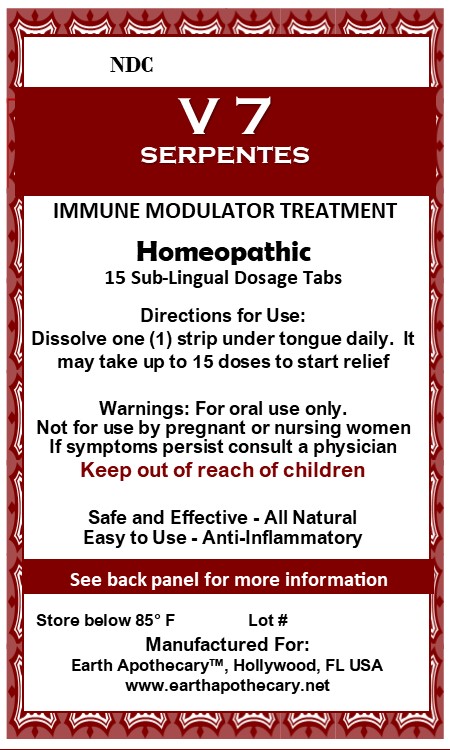 DRUG LABEL: V 7 SERPENTES
NDC: 72295-002 | Form: STRIP
Manufacturer: Essentials Complementary Wellness Center
Category: homeopathic | Type: HUMAN OTC DRUG LABEL
Date: 20180502

ACTIVE INGREDIENTS: NAJA NAJA VENOM 10 [hp_X]/1 [hp_X]
INACTIVE INGREDIENTS: SODIUM CHLORIDE; WATER; THIMEROSAL; CARBOXYMETHYLCELLULOSE; SUCROSE; ORANGE OIL

V 7 SERPENTES Immune Modulatory Treatment

WARNINGS

For oral use only

If symptoms persist stop using this product and consult a physician

Side effects may include headache, nausea, sore throat

Keep out of reach of children

ACTIVE INGREDIENT

Naja Naja H 10X

INACTIVE INGREDIENT

Carboxymethyelcellulose, sodium chloride 0.9%, water, natural orange flavorings, sucrose , thimerosol

PURPOSE

Immune Modulator

PREGNANCY OR BREAST FEEDING

Not for use by pregnant or nursing women

Uses

Temporarily reduces joint inflammation and pain and general associated pain.

Directions for Use

Dissolve one (1) strip under tongue daily. It may take up to 15 doses to start relief.

Directions for Use

- Open foil pouch
- place one (1) tab under tongue to dissolve
- allow the tab to dissolve completely (about 30 seconds)
- do not swallow tab
- allow several days for the drug to take effect
- no food or water 10 min before or after dose